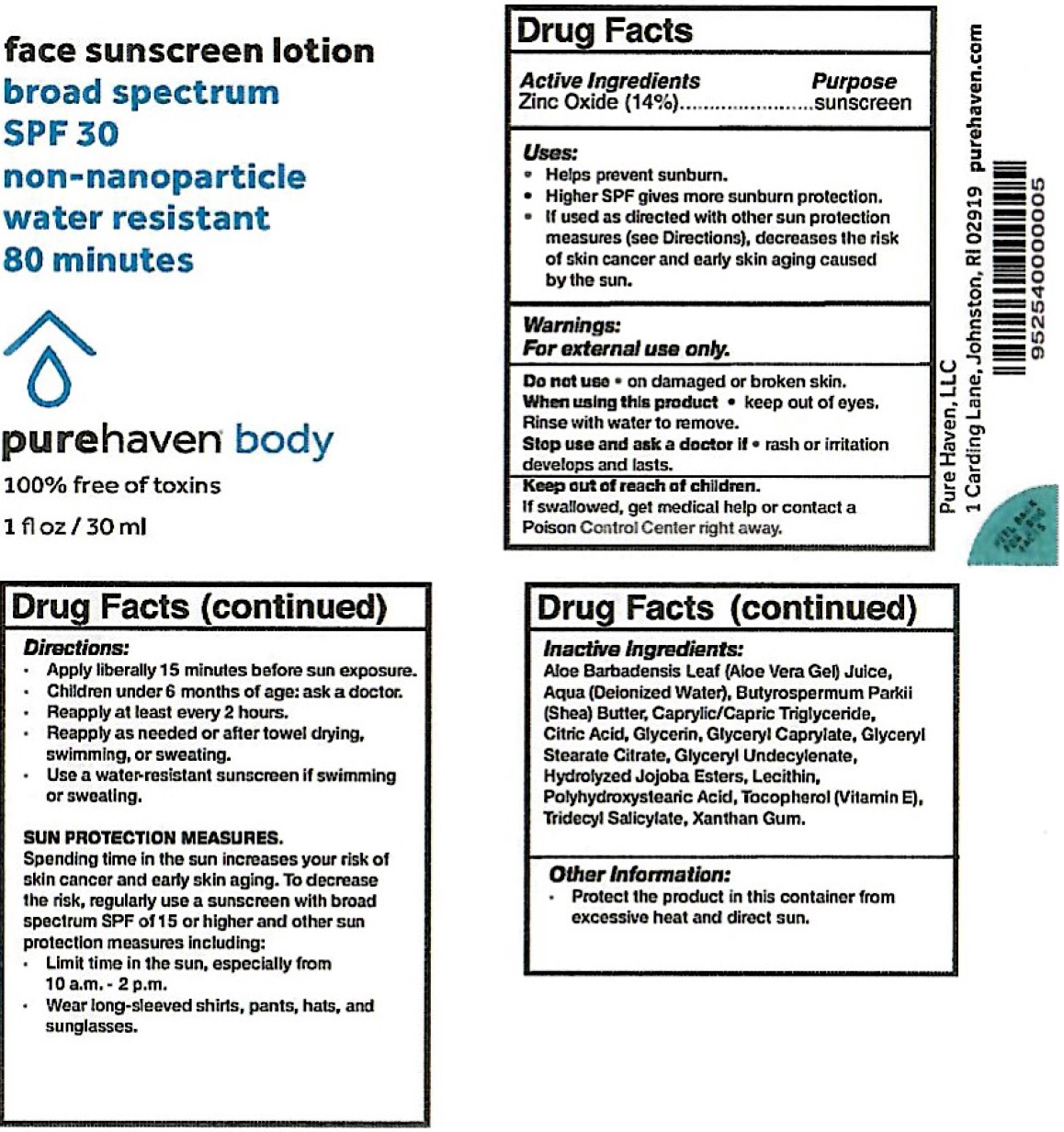 DRUG LABEL: PURE HAVEN Face Sunscreen SPF-30
NDC: 71355-219 | Form: LOTION
Manufacturer: Pure Haven, LLC
Category: otc | Type: HUMAN OTC DRUG LABEL
Date: 20231111

ACTIVE INGREDIENTS: ZINC OXIDE 140 mg/1 mL
INACTIVE INGREDIENTS: ALOE VERA LEAF; WATER; SHEA BUTTER; MEDIUM-CHAIN TRIGLYCERIDES; CITRIC ACID MONOHYDRATE; GLYCERIN; GLYCERYL MONOCAPRYLATE; GLYCERYL STEARATE CITRATE; GLYCERYL 1-UNDECYLENATE; HYDROLYZED JOJOBA ESTERS (ACID FORM); TOCOPHEROL; TRIDECYL SALICYLATE; XANTHAN GUM

PURE HAVEN Face Sunscreen Lotion SPF-30

Active Ingredients

Zinc Oxide (14%)

Purpose

sunscreen

Uses:

- Helps prevent sunburn.
- Higher SPF gives more sunburn protection.
- If used as directed with other sun protection measures (See Directions), decreases the risk of skin cancer and early skin aging caused by the sun.

Warnings:

For external use only.

Do not use

- on damaged or broken skin.

When using this product

- keep out of eyes. Rinse with water to remove.

Stop use and ask a doctor if

- rash or irritation develops and lasts.

Keep out of reach of children.

If swallowed, get medical help or contact a Poison Control Center right away.

Directions:

- Apply liberally 15 minutes before sun exposure.
- Children under 6 months of age: ask a doctor.
- Reapply at least every 2 hours.
- Reapply as needed or after towel drying, swimming, or sweating.
- Use a water-resistant sunscreen if swimming or sweating.

- Limit time in the sun, especially from 10 a.m. - 2 p.m.
- Wear long-sleeved shirts, pants, hats and sunglasses.

SUN PROTECTION MEASURES.

Spending time in the sun increases your risk of skin cancer and early skin aging. To decrease the risk, regularly use a sunscreen with broad spectrum SPF of 15 or higher and other sun protection measures including:

Inactive Ingredients:

Aloe Barbadensis Leaf (Aloe Vera Gel) Juice, Aqua (Deionized Water), Butyrospermum Parkii (Shea) Butter, Caprylic/Capric Triglyceride, Citric Acid, Glycerin, Glyceryl Caprylate, Glyceryl Stearate Citrate, Glyceryl Undecylenate, Hydrolyzed Jojoba Esters, Lecithin, Polyhydroxystearic Acid, Tocopherol (Vitamin E),Tridecyl Salicylate, Xanthan Gum.

Other Information:

- Protect the product in this container from excessive heat and direct sun.